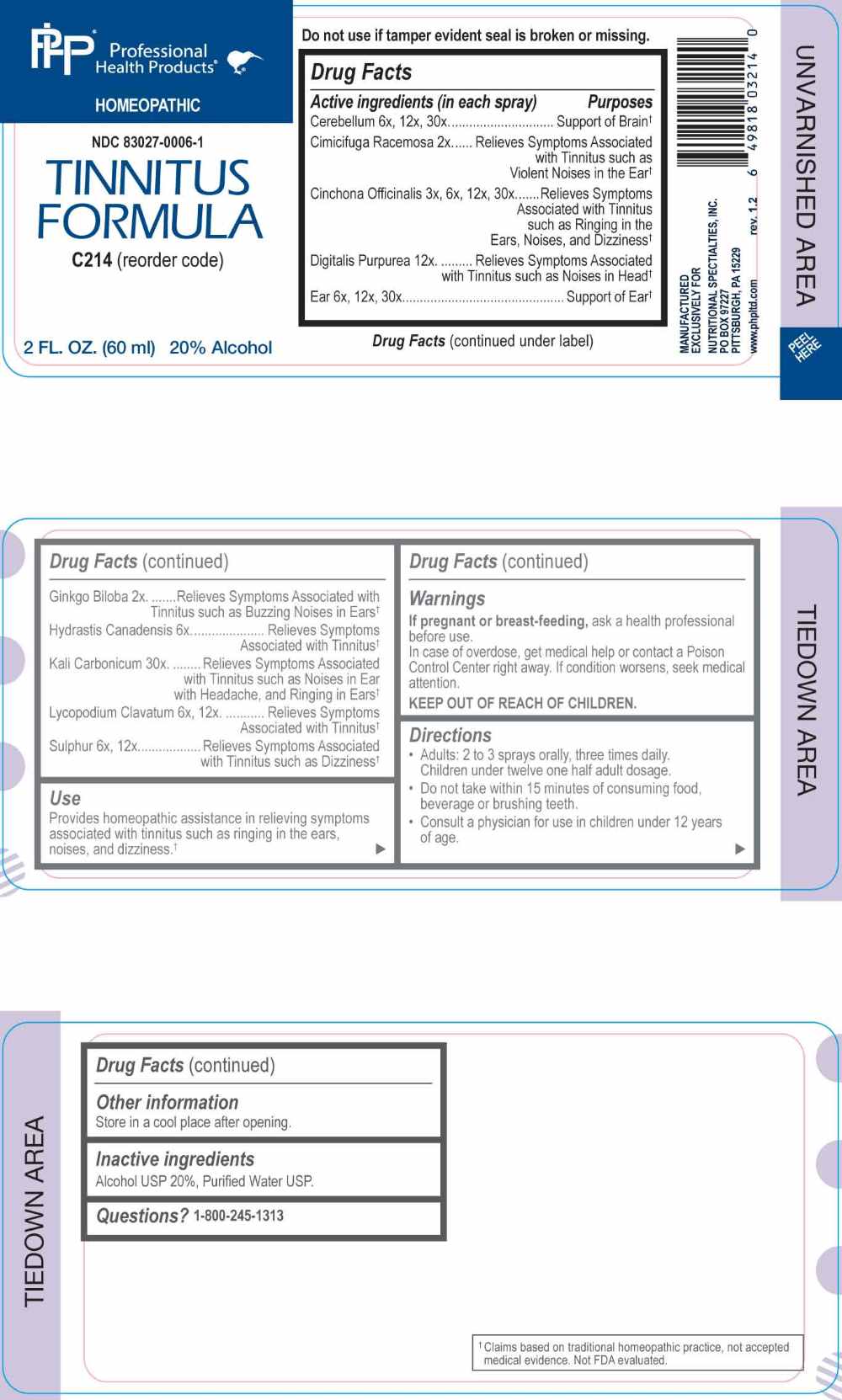 DRUG LABEL: Tinnitus Formula
NDC: 83027-0006 | Form: SPRAY
Manufacturer: Nutritional Specialties, Inc.
Category: homeopathic | Type: HUMAN OTC DRUG LABEL
Date: 20251006

ACTIVE INGREDIENTS: BLACK COHOSH 2 [hp_X]/1 mL; GINKGO 2 [hp_X]/1 mL; CINCHONA OFFICINALIS BARK 3 [hp_X]/1 mL; GOLDENSEAL 6 [hp_X]/1 mL; LYCOPODIUM CLAVATUM SPORE 6 [hp_X]/1 mL; SULFUR 6 [hp_X]/1 mL; SUS SCROFA CEREBRUM 6 [hp_X]/1 mL; SUS SCROFA EAR 6 [hp_X]/1 mL; DIGITALIS 12 [hp_X]/1 mL; POTASSIUM CARBONATE 30 [hp_X]/1 mL
INACTIVE INGREDIENTS: WATER; ALCOHOL

DRUG FACTS:

ACTIVE INGREDIENTS:

Cerebellum 6X, 12X, 30X, Cimicifuga Racemosa 2X, Cinchona Officinalis 3X, 6X, 12X, 30X, Digitalis Purpurea 12X, Ear 6X, 12X, 30X, Ginkgo Biloba 2X, Hydrastis Canadensis 6X, Kali Carbonicum 30X, Lycopodium Clavatum 6X, 12X, Sulphur 6X, 12X.

PURPOSE:

Cerebellum- Support of Brain,† Cimicifuga Racemosa – Relieves Symptoms Associated with Tinnitus such as Violent Noises in the Ear,† Cinchona Officinalis - Relieves Symptoms Associated with Tinnitus such as ringing in the Ears, Noises, and Dizziness,† Digitalis Purpurea - Relieves Symptoms Associated with Tinnitus such as Noises in Head,† Ear – Support of Ear,† Ginkgo Biloba - Relieves Symptoms Associated with Tinnitus such as Buzzing Noises in Ears,† Hydrastis Canadensis – Relieves Symptoms Associated with Tinnitus,† Kali Carbonicum - Relieves Symptoms Associated with Tinnitus such as Noises in Ear with Headache, and Ringing in Ears,† Lycopodium Clavatum – Relieves Symptoms Associated with Tinnitus,† Sulphur – Relieves Symptoms Associated with Tinnitus such as Dizziness†

†Claims based on traditional homeopathic practice, not accepted medical evidence. Not FDA evaluated.

USES:

Provides homeopathic assistance in relieving symptoms associated with tinnitus such as ringing in the ears, noises, and dizziness.†

†Claims based on traditional homeopathic practice, not accepted medical evidence. Not FDA evaluated.

WARNINGS:

If pregnant or breast-feeding, ask a health professional before use.

In case of overdose, get medical help or contact a Poison Control Center right away.

If condition worsens, seek medical attention.

KEEP OUT OF REACH OF CHILDREN

Do not use if tamper evident seal is broken or missing.

Store in a cool place after opening

KEEP OUT OF REACH OF CHILDREN:

In case of overdose, get medical help or contact a Poison Control Center right away.

DIRECTIONS:

• Adults: 2 to 3 sprays orally, three times daily. Children under twelve one half adult dosage.

• Do not take within 15 minutes of consuming food, beverage or brushing teeth.

Consult a physician for use in children under 12 years of age.

INACTIVE INGREDIENTS:

Alcohol USP 20%, Purified Water USP.

QUESTIONS:

MANUFACTURED EXCLUSIVELY FOR

NUTRITIONAL SPECIALTIES, INC.

PO BOX 97227

PITTSBURG, PA 15229

www.phpltd.com

1-800-245-1313

PACKAGE LABEL DISPLAY:

Professional

Health Products

HOMEOPATHIC

NDC 83027-0006-1

TINNITUS FORMULA

2 FL. OZ (60 ml)